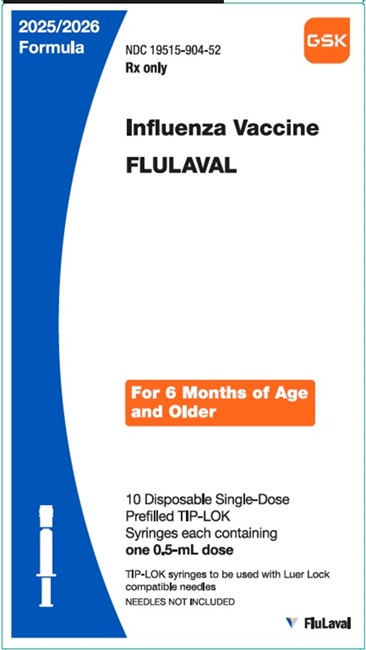 DRUG LABEL: FLULAVAL
NDC: 19515-904 | Form: SUSPENSION
Manufacturer: ID Biomedical Corporation of Quebec
Category: other | Type: VACCINE LABEL
Date: 20250701

ACTIVE INGREDIENTS: INFLUENZA A VIRUS A/VICTORIA/4897/2022 IVR-238 (H1N1) ANTIGEN (UV, FORMALDEHYDE INACTIVATED) 15 ug/0.5 mL; INFLUENZA A VIRUS A/Croatia/10136RV/2023 X-425A (H3N2) ANTIGEN (UV, FORMALDEHYDE INACTIVATED) 15 ug/0.5 mL; INFLUENZA B VIRUS B/AUSTRIA/1359417/2021 BVR-26 ANTIGEN (UV, FORMALDEHYDE INACTIVATED) 15 ug/0.5 mL
INACTIVE INGREDIENTS: SODIUM CHLORIDE; SODIUM PHOSPHATE, DIBASIC, HEPTAHYDRATE; MONOBASIC POTASSIUM PHOSPHATE; POTASSIUM CHLORIDE; .ALPHA.-TOCOPHEROL SUCCINATE, D-; POLYSORBATE 80; WATER

HIGHLIGHTS OF PRESCRIBING INFORMATION

These highlights do not include all the information needed to use FLULAVAL safely and effectively. See full prescribing information for FLULAVAL.
FLULAVAL (Influenza Vaccine)
Injectable Suspension, for Intramuscular Use
2025-2026 Formula
Initial U.S. Approval: 2006

1 INDICATIONS AND USAGE

FLULAVAL is a vaccine indicated for active immunization for the prevention of disease caused by influenza A subtype viruses and type B virus contained in the vaccine. FLULAVAL is approved for use in persons aged 6 months and older. (1)

2 DOSAGE AND ADMINISTRATION

For intramuscular use. (2)

Age | Vaccination Status | Dose and Schedule
6 months through 8 years | Not previously vaccinated with influenza vaccine | Two doses (0.5 mL each) at least 4 weeks apart (2.1)
6 months through 8 years | Vaccinated with influenza vaccine in a previous season | One or 2 dosesa (0.5 mL each) (2.1)
9 years and older | Not applicable | One 0.5‑mL dose (2.1)
a One dose or 2 doses (0.5 mL each) depending on vaccination history as per the annual Advisory Committee on Immunization Practices (ACIP) recommendation on prevention and control of seasonal influenza with vaccines. If 2 doses, administer each 0.5-mL dose at least 4 weeks apart. (2.1)

3 DOSAGE FORMS AND STRENGTHS

FLULAVAL is an injectable suspension. A single dose is 0.5 mL. (3)

4 CONTRAINDICATIONS

Do not administer FLULAVAL to anyone with a history of severe allergic reactions (e.g., anaphylaxis) to any component of the vaccine, including egg protein, or following a previous dose of any influenza vaccine. (4, 11)

5 WARNINGS AND PRECAUTIONS

- If Guillain-Barré syndrome has occurred within 6 weeks of receipt of a prior influenza vaccine, the decision to give FLULAVAL should be based on careful consideration of the potential benefits and risks. (5.1)
- Syncope (fainting) can occur in association with administration of injectable vaccines, including FLULAVAL. Procedures should be in place to avoid injury from fainting. (5.2)

6 ADVERSE REACTIONS

- In adults who received FLULAVAL, the most common (≥10%) solicited local adverse reactions were pain (51%), redness (13%), and/or swelling (11%); the most common solicited systemic adverse reactions were fatigue (20%), headache (18%), and muscle aches/arthralgia (18%). (6.1)
- In children aged 3 through 17 years who received FLULAVAL, the most common (≥10%) solicited local adverse reaction was pain (56%). (6.1)
- In children aged 3 through 4 years who received FLULAVAL, the most common (≥10%) solicited systemic adverse reactions were irritability (25%), drowsiness (19%), and loss of appetite (16%). (6.1)
- In children aged 5 through 17 years who received FLULAVAL, the most common (≥10%) solicited systemic adverse reactions were muscle aches (24%), headache (17%), and fatigue (17%). (6.1)
- In children aged 6 through 35 months who received FLULAVAL QUADRIVALENT, the most common (≥10%) solicited local adverse reaction was pain (40%); most common solicited systemic adverse reactions were irritability (49%), drowsiness (37%), and loss of appetite (29%). (6.1)

To report SUSPECTED ADVERSE REACTIONS, contact GlaxoSmithKline at 1-888-825-5249 or VAERS at 1-800-822-7967 or www.vaers.hhs.gov.

8 USE IN SPECIFIC POPULATIONS

- Geriatric Use: Antibody responses were lower in geriatric subjects who received FLULAVAL than in younger subjects. (8.5)

FULL PRESCRIBING INFORMATION

1 INDICATIONS AND USAGE

FLULAVAL is indicated for active immunization for the prevention of disease caused by influenza A subtype viruses and type B virus contained in the vaccine. FLULAVAL is approved for use in persons aged 6 months and older.

2 DOSAGE AND ADMINISTRATION

For intramuscular use.

2.1 Dosage and Schedule

The dose and schedule for FLULAVAL are presented in Table 1.

Table 1. FLULAVAL: Dosing
Age | Vaccination Status | Dose and Schedule
6 months through 8 years | Not previously vaccinated with influenza vaccine | Two doses (0.5 mL each) at least 4 weeks apart
6 months through 8 years | Vaccinated with influenza vaccine in a previous season | One or 2 dosesa (0.5 mL each)
9 years and older | Not applicable | One 0.5‑mL dose
a One dose or 2 doses (0.5 mL each) depending on vaccination history as per the annual Advisory Committee on Immunization Practices (ACIP) recommendation on prevention and control of seasonal influenza with vaccines. If 2 doses, administer each 0.5‑mL dose at least 4 weeks apart.

2.2 Administration Instructions

Shake well before administration. Parenteral drug products should be inspected visually for particulate matter and discoloration prior to administration, whenever solution and container permit. If either of these conditions exists, the vaccine should not be administered.

Attach a sterile needle to the prefilled syringe and administer intramuscularly.

3 DOSAGE FORMS AND STRENGTHS

FLULAVAL is an injectable suspension. A single dose is 0.5 mL.

4 CONTRAINDICATIONS

Do not administer FLULAVAL to anyone with a history of severe allergic reactions (e.g., anaphylaxis) to any component of the vaccine, including egg protein, or following a previous dose of any influenza vaccine [see Description (11)].

5 WARNINGS AND PRECAUTIONS

5.1 Guillain-Barré Syndrome

If Guillain-Barré syndrome (GBS) has occurred within 6 weeks of receipt of a prior influenza vaccine, the decision to give FLULAVAL should be based on careful consideration of the potential benefits and risks.

The 1976 swine influenza vaccine was associated with an elevated risk of GBS. Evidence for a causal relation of GBS with other influenza vaccines is inconclusive; if an excess risk exists, it is probably slightly more than 1 additional case/1 million persons vaccinated.

5.2 Syncope

Syncope (fainting) may occur in association with administration of injectable vaccines, including FLULAVAL. Procedures should be in place to avoid injury from fainting.

5.3 Preventing and Managing Allergic Vaccine Reactions

Appropriate medical treatment must be immediately available to manage potential anaphylactic reactions following administration of FLULAVAL.

5.4 Altered Immunocompetence

If FLULAVAL is administered to immunosuppressed persons, including individuals receiving immunosuppressive therapy, the immune response may be lower than in immunocompetent persons.

5.5 Limitations of Vaccine Effectiveness

Vaccination with FLULAVAL may not protect all susceptible individuals.

6 ADVERSE REACTIONS

In adults who received FLULAVAL, the most common (≥10%) solicited local adverse reactions were pain (51%), redness (13%), and swelling (11%); the most common (≥10%) solicited systemic adverse reactions were fatigue (20%), headache (18%), and muscle aches/arthralgia (18%).

In children aged 3 through 17 years who received FLULAVAL, the most common (≥10%) solicited local adverse reaction was pain (56%). In children aged 3 through 4 years, the most common (≥10%) solicited systemic adverse reactions were irritability (25%), drowsiness (19%), and loss of appetite (16%). In children aged 5 through 17 years, the most common (≥10%) systemic adverse reactions were muscle aches (24%), headache (17%), and fatigue (17%).

In children aged 6 through 35 months who received FLULAVAL QUADRIVALENT, the most common (≥10%) solicited local adverse reaction was pain (40%); the most common (≥10%) solicited systemic adverse reactions were irritability (49%), drowsiness (37%), and loss of appetite (29%). Data with FLULAVAL QUADRIVALENT are relevant to FLULAVAL because both vaccines are manufactured using the same process and have overlapping compositions.

6.1 Clinical Trials Experience

Because clinical trials are conducted under widely varying conditions, adverse reaction rates observed in the clinical trials of a vaccine cannot be directly compared with rates in the clinical trials of another vaccine, and may not reflect the rates observed in practice. There is the possibility that broad use of FLULAVAL could reveal adverse reactions not observed in clinical trials.

FLULAVAL has been administered in 3 trials to 5,114 individuals aged 18 years and older, and 1 trial to 987 individuals aged 3 through 17 years. FLULAVAL QUADRIVALENT has been administered in 1 trial to 1,207 individuals aged 6 through 35 months.

FLULAVAL in Adults

Safety data were obtained from 3 randomized, controlled trials, one of which was a placebo-controlled efficacy trial. In these trials, 9,836 subjects were randomized to receive either FLULAVAL (5,114 subjects in the safety analysis), FLUZONE, a U.S.‑licensed trivalent, inactivated influenza vaccine, manufactured by Sanofi Pasteur Inc. (894 subjects in the safety analysis), or placebo (3,828 subjects in the safety analysis), intramuscularly. In these trials, solicited reactions were collected for 4 days (i.e., 30 minutes post-vaccination through the next 3 days). Unsolicited adverse events that occurred within 22 days of vaccination (Day 0 to 21) were recorded based on spontaneous reports or in response to queries about changes in health status.

Trial 1 (NCT01389479): Safety information was collected in a randomized, controlled US trial. This trial included 1,000 adults aged 18 through 64 years who were randomized to receive FLULAVAL (n = 721) or a U.S. ‑licensed trivalent, inactivated influenza vaccine (n = 279). Among recipients of FLULAVAL, 57% were female; 91% of subjects were white and 9% were of other racial/ethnic groups. The mean age of subjects was 38 years; 80% were aged 18 through 49 years and 20% were aged 50 through 64 years.

Trial 2 (NCT00232947): Safety information was collected in a randomized, double-blind, active-controlled U.S. trial. The trial included 1,225 adults aged ≥50 years randomized to receive FLULAVAL (n = 610) or a U.S.‑licensed trivalent, inactivated influenza vaccine (n = 615). In the total population, 57% were female; 95% of subjects were white and 5% were of other racial/ethnic groups. The mean age of subjects was 66 years; 46% were aged 50 through 64 years, 41% were aged 65 through 79 years, and 13% were aged ≥80 years.

Trial 3 (NCT00216242): Safety information was collected in a double-blind, placebo-controlled U.S. trial. The trial included 7,658 adults aged 18 through 49 years randomized to receive FLULAVAL (n = 3,807) or placebo (n = 3,851). In the total population, 61% were female; 84% of subjects were white, 10% black, 2% Asian, and 4% were of other racial/ethnic groups. The mean age of subjects was 33 years.

Solicited Adverse Reactions: Solicited adverse reactions collected in trials 1, 2, and 3 for 4 days (day of vaccination and the next 3 days) are presented in Table 2.

Table 2. FLULAVAL: Incidence of Solicited Local and Systemic Adverse Reactions within 4 Daysa of Vaccination in Adults (Total Vaccinated Cohort)
Adverse Reactions | Trial 1b; Aged 18 through 64 Years |  |  |  | Trial 2b; Aged 50 Years and Older |  |  |  | Trial 3b; Aged 18 through 49 Years
Adverse Reactions | FLULAVAL |  | Comparatorc |  | FLULAVAL |  | Comparatorc |  | FLULAVAL |  | Placebo
Adverse Reactions | n = 721; % |  | n = 279; % |  | n = 610; % |  | n = 615; % |  | n = 3,783; % |  | n = 3,828; %
 | Any | Gr 3d | Any | Gr 3d | Any | Gr 3d | Any | Gr 3d | Any | Gr 3d | Any | Gr 3d
Local
Pain | 24 | 0 | 31 | 0.4 | 25 | 0 | 32 | 0 | 51 | 0.2 | 14 | <0.1
Redness | 11 | 0.1 | 10 | 0 | 10 | 0.2 | 11 | 0.2 | 13 | 0.3 | 6 | 0.1
Swelling | 10 | 0.1 | 10 | 0.4 | 7 | 0.3 | 9 | 1 | 11 | 0.3 | 3 | 0
Systemic
Headache | 18 | 0.4 | 17 | 0 | 11 | 0.2 | 12 | 0.3 | 18 | 1 | 19 | 1
Fatigue | 17 | 0.3 | 15 | 0 | 12 | 0.2 | 13 | 1 | 20 | 1 | 18 | 0.4
Muscle achese | 13 | 0.4 | 16 | 0 | 11 | 0.2 | 10 | 0 | 18 | 0.2 | 10 | 0.2
Feverf | 11 | 0 | 10 | 0.4 | 1 | 0 | 2 | 0 | 3 | <0.1 | 1 | 0.1
Malaise | 10 | 0.4 | 10 | 0.4 | 6 | 0.3 | 7 | 0 | 9 | 0.3 | 6 | 0.4
Sore throat | 9 | 0.4 | 9 | 0 | 5 | 0.2 | 6 | 0 | 9 | 0.3 | 9 | 0.4
Reddened eyes | 6 | 0.3 | 5 | 0 | 4 | 0 | 7 | 0 | 7 | <0.1 | 6 | <0.1
Cough | 6 | 0.3 | 7 | 0 | 5 | 0.2 | 6 | 0 | 8 | 0.1 | 7 | 0.1
Chills | 5 | 0.3 | 2 | 0 | 3 | 0.2 | 6 | 0 | 4 | 0.2 | 4 | 0.2
Chest tightness | 3 | 0 | 1 | 0 | 3 | 0.3 | 2 | 0 | 3 | <0.1 | 3 | 0.1
Facial swelling | 1 | 0 | 0.4 | 0 | 1 | 0 | 2 | 0 | 1 | 0 | 1 | 0
Total vaccinated cohort for safety included all vaccinated subjects for whom safety data were available. n = number of subjects with diary card completed. Gr 3 = Grade 3. Values ≥0.5 have been rounded to the nearest integer.
a Four days included day of vaccination and the subsequent 3 days.
b Trial 1: NCT01389479; Trial 2: NCT00232947; Trial 3: NCT00216242.
c U.S.-licensed trivalent, inactivated influenza vaccine (manufactured by Sanofi Pasteur Inc.).
d Grade 3 pain, headache, fatigue, muscle aches, malaise, sore throat, cough, chills, chest tightness: Defined as prevented work/school/normal activities.
Grade 3 redness, swelling: Defined as >50 mm. Grade 3 fever: Defined as >103.1°F (39.5°C).
Grade 3 reddened eyes: Defined as very reddened, interfered with vision or caused a doctor’s visit. Grade 3 facial swelling: Defined as very swollen, prevented work/school/normal activities or caused a doctor’s visit.
e For Trial 2 and Trial 3, includes muscle aches and arthralgia.
f Fever: Defined as ≥99.5°F (37.5°C).

Unsolicited Adverse Events: The incidence of unsolicited adverse events in the 21 days post-vaccination was comparable for FLULAVAL and the active comparator in Trial 1 (16% and 15%, respectively) and in Trial 2 (18% and 21%, respectively). In Trial 3, the incidence of unsolicited adverse events was comparable for the groups (21% for FLULAVAL and 19% for placebo).

Unsolicited adverse events defined as reported with FLULAVAL in >1.0% of subjects are described as follows: Trial 1: Cough, headache, and pharyngolaryngeal pain; Trial 2: Diarrhea, headache, and nasopharyngitis; and Trial 3: Pharyngolaryngeal pain, headache, fatigue, cough, injection site pain, upper respiratory tract infection, musculoskeletal pain, nasopharyngitis, injection site erythema, and discomfort.

Serious Adverse Events (SAEs): In Trial 1, no SAEs were reported. In Trial 2, 3% of subjects receiving FLULAVAL and 3% of subjects receiving the active comparator reported SAEs. In Trial 3, 1% of subjects receiving FLULAVAL and 1% of subjects receiving placebo reported SAEs. In the 3 clinical trials, the rates of SAEs were comparable between groups and none of the SAEs were considered related to vaccination.

FLULAVAL in Children

Trial 4 (NCT00980005) (Immunogenicity Non-Inferiority): An observer-blind, active-controlled U.S. trial evaluated subjects aged 3 through 17 years who received FLULAVAL (n = 1,055) or FLUZONE (n = 1,061), a U.S.‑licensed trivalent, inactivated influenza vaccine, manufactured by Sanofi Pasteur Inc. In the overall population, 53% were male; 78% of subjects were white, 12% were black, 2% were Asian, and 8% were of other racial/ethnic groups. The mean age of subjects was 8 years. Children aged 3 through 8 years with no history of influenza vaccination received 2 doses approximately 28 days apart. Children aged 3 through 8 years with a history of influenza vaccination and children aged 9 years and older received one dose. Solicited adverse reactions were collected for 4 days (day of vaccination and the next 3 days) (Table 3).

Table 3. FLULAVAL: Incidence of Solicited Local and Systemic Adverse Reactions within 4 Daysa of First Vaccination in Children Aged 3 through 17 Yearsb (Total Vaccinated Cohort)
Adverse Reactions | FLULAVAL; % |  | Active Comparatorc; %
Adverse Reactions | Any | Grade 3d | Any | Grade 3d
Adverse Reactions | Aged 3 through 17 Years
Local | n = 1,042 |  | n = 1,026
Pain | 56 | 2 | 53 | 2
Redness | 4 | 0.2 | 5 | 0
Swelling | 4 | 0.1 | 5 | 0
 | Aged 3 through 4 Years
Systemic | n = 293 |  | n = 279
Irritability | 25 | 2 | 27 | 1
Drowsiness | 19 | 1 | 19 | 0.4
Loss of appetite | 16 | 2 | 13 | 0.4
Fevere | 5 | 1 | 3 | 0.4
 | Aged 5 through 17 Years
Systemic | n = 750 |  | n = 747
Muscle aches | 24 | 1 | 23 | 1
Headache | 17 | 1 | 15 | 1
Fatigue | 17 | 1 | 17 | 1
Arthralgia | 8 | 0.3 | 10 | 0.3
Shivering | 6 | 0.1 | 5 | 0.4
Fevere | 5 | 2 | 4 | 2
Total vaccinated cohort for safety included all vaccinated subjects for whom safety data were available. n = number of subjects with diary card completed. Values ≥0.5 have been rounded to the nearest integer.
a Four days included day of vaccination and the subsequent 3 days.
b Trial 4: NCT00980005.
c U.S.-licensed trivalent, inactivated influenza vaccine (manufactured by Sanofi Pasteur Inc.).
d Grade 3 pain: Defined as cried when limb was moved/spontaneously painful (children <5years), or pain that prevented normal activity (children ≥5 years).
Grade 3 swelling, redness: Defined as >100 mm.
Grade 3 irritability, drowsiness, muscle aches, headache, fatigue, arthralgia, shivering: Defined as prevented normal activity.
Grade 3 loss of appetite: Defined as not eating at all.
Grade 3 (or higher) fever: Defined as ≥102.2°F (39.0°C).
e Fever: Defined as ≥100.4°F (38.0°C)

In children who received a second dose of FLULAVAL or the comparator vaccine, the incidences of adverse reactions following the second dose were generally lower than those observed after the first dose.

The incidence of unsolicited adverse events that occurred within 28 days (Day 0 to 27) of any vaccination reported in subjects who received FLULAVAL (n = 1,055) or FLUZONE (n = 1,061) was 40% and 37%, respectively. The unsolicited adverse events that occurred most frequently (≥0.1% of subjects for FLULAVAL) and considered possibly related to vaccination included diarrhea, influenza-like illness, injection site hematoma, injection site rash, injection site warmth, rash, upper abdominal pain, and vomiting. The rates of SAEs were comparable between groups (0.9% and 0.6% for FLULAVAL and the comparator, respectively); none of the SAEs were considered related to vaccination.

FLULAVAL QUADRIVALENT in Children

Safety data were obtained with FLULAVAL QUADRIVALENT in children aged 6 through 35 months. Data with FLULAVAL QUADRIVALENT are relevant to FLULAVAL because both vaccines are manufactured using the same process and have overlapping compositions.

Trial 5 (NCT02242643) was a randomized, observer-blind, active-controlled immunogenicity and safety trial. The trial included subjects aged 6 through 35 months who received FLULAVAL QUADRIVALENT (n = 1,207) or FLUZONE QUADRIVALENT, a U.S.-licensed inactivated influenza vaccine (n = 1,217) used as comparator, manufactured by Sanofi Pasteur Inc. Children with no history of influenza vaccination received 2 doses of FLULAVAL QUADRIVALENT or the comparator vaccine approximately 28 days apart. Children with a history of influenza vaccination received one dose of FLULAVAL QUADRIVALENT or the comparator vaccine. In the overall population, 53% were male; 64% were white, 16% were black, 3% were Asian, and 17% were of other racial/ethnic groups. The mean age of subjects was 20 months. Subjects were followed for safety for 6 months; solicited adverse reactions were collected for 7 days (day of vaccination and the next 6 days) postvaccination. The incidence of solicited adverse reactions occurring within 7 days of vaccination in children are shown in Table 4.

Table 4. FLULAVAL QUADRIVALENT: Incidence of Solicited Local and Systemic Adverse Reactions within 7 Daysa of First Vaccination in Children Aged 6 through 35 Monthsb (Total Vaccinated Cohort)
Adverse Reactions | FLULAVAL QUADRIVALENT; % |  | Active Comparatorc; %
Adverse Reactions | Any | Grade 3d | Any | Grade 3d
Local | n = 1,151 |  | n = 1,146
Pain | 40 | 2 | 37 | 1
Swelling | 1 | 0 | 0.4 | 0
Redness | 1 | 0 | 1 | 0
Systemic | n = 1,155 |  | n = 1,148
Irritability | 49 | 4 | 46 | 3
Drowsiness | 37 | 3 | 37 | 3
Loss of appetite | 29 | 2 | 29 | 1
Fevere | 6 | 1 | 6 | 1
Total vaccinated cohort for safety included all vaccinated subjects for whom safety data were available (i.e., diary card completed for solicited symptoms). n = number of subjects with diary card completed. Values ≥0.5 have been rounded to the nearest integer.
a Seven days included day of vaccination and the subsequent 6 days.
b Trial 5: NCT02242643.
c U.S.‑licensed quadrivalent, inactivated influenza vaccine (manufactured by Sanofi Pasteur Inc.).
d Grade 3 pain: Defined as cried when limb was moved/spontaneously painful.
Grade 3 swelling, redness: Defined as >100 mm.
Grade 3 irritability: Defined as crying that could not be comforted/prevented normal activity.
Grade 3 drowsiness: Defined as prevented normal activity.
Grade 3 loss of appetite: Defined as not eating at all.
Grade 3 (or higher) fever: Defined as >102.2°F (39.0°C).
e Fever: Defined as ≥100.4°F (38.0°C).

In children who received a second dose of FLULAVAL QUADRIVALENT or the comparator vaccine, the incidences of solicited adverse reactions following the second dose were generally similar or lower than those observed after the first dose.

Unsolicited adverse events occurring within 28 days of vaccination were reported in 46% and 44% of subjects who received FLULAVAL QUADRIVALENT (n = 1,207) and the comparator vaccine (n = 1,217), respectively. The unsolicited adverse reactions that occurred most frequently (≥1%) for FLULAVAL QUADRIVALENT included upper respiratory tract infection, cough, diarrhea, pyrexia, vomiting, and rash. Serious adverse events occurring during the study period (approximately 6 months) were reported in 2% of subjects who received FLULAVAL QUADRIVALENT and in 2% of subjects who received the comparator vaccine. There were no deaths reported during the study period.

6.2 Postmarketing Experience

The following adverse reactions have been identified during postapproval use of FLULAVAL or FLUAVAL QUADRIVALENT. Because these reactions are reported voluntarily from a population of uncertain size, it is not always possible to reliably estimate their frequency or establish a causal relationship to the vaccine.

Blood and Lymphatic System Disorders

Lymphadenopathy.

Eye Disorders

Eye pain, photophobia.

Gastrointestinal Disorders

Dysphagia, vomiting.

General Disorders and Administration Site Conditions

Chest pain, injection site inflammation, asthenia, injection site rash, abnormal gait, injection site bruising, injection site sterile abscess, influenza-like symptoms.

Immune System Disorders

Allergic reactions including anaphylaxis, angioedema.

Infections and Infestations

Rhinitis, laryngitis, cellulitis.

Musculoskeletal and Connective Tissue Disorders

Muscle weakness, arthritis.

Nervous System Disorders

Dizziness, paresthesia, hypoesthesia, hypokinesia, tremor, somnolence, syncope, Guillain-Barré syndrome, convulsions/seizures, facial or cranial nerve paralysis, encephalopathy, limb paralysis.

Psychiatric Disorders

Insomnia.

Respiratory, Thoracic, and Mediastinal Disorders

Dyspnea, dysphonia, bronchospasm, throat tightness.

Skin and Subcutaneous Tissue Disorders

Urticaria, pruritus, sweating, localized or generalized rash.

Vascular Disorders

Flushing, pallor.

8 USE IN SPECIFIC POPULATIONS

8.1 Pregnancy

Risk Summary

All pregnancies have a risk of birth defect, loss, or other adverse outcomes. In the U.S. general population, the estimated background risk of major birth defects and miscarriage in clinically recognized pregnancies is 2% to 4% and 15% to 20%, respectively.

There are insufficient data on FLULAVAL in pregnant women to inform vaccine-associated risks.

A developmental toxicity study was performed in female rats administered FLULAVAL prior to mating and during gestation. Animals were administered a total dose of 0.2 mL on each of five occasions (a single human dose is 0.5 mL). This study revealed no adverse effects on fetal or pre-weaning development due to FLULAVAL [see Data].

Clinical Considerations

Disease-Associated Maternal and/or Embryo/Fetal Risk: Pregnant women infected with seasonal influenza are at increased risk of severe illness associated with influenza infection compared with non-pregnant women. Pregnant women with influenza may be at increased risk for adverse pregnancy outcomes, including preterm labor and delivery.

Data

Animal Data: In a developmental toxicity study, female rats were administered FLULAVAL by intramuscular injection 4 weeks prior to mating, and on gestation Days 6, 8, 11, and 15. The total dose was 0.2 mL at each occasion (a single human dose is 0.5 mL). No adverse effects on pre-weaning development up to post-natal Day 25 were observed. There were no vaccine-related fetal malformations or variations, or vaccine-related effects on female fertility.

8.2 Lactation

Risk Summary

It is not known whether FLULAVAL is excreted in human milk. Data are not available to assess the effects of FLULAVAL on the breastfed infant or on milk production/excretion. The developmental and health benefits of breastfeeding should be considered along with the mother’s clinical need for FLULAVAL and any potential adverse effects on the breastfed child from FLULAVAL or from the underlying maternal condition. For preventive vaccines, the underlying maternal condition is susceptibility to disease prevented by the vaccine.

8.4 Pediatric Use

Safety and effectiveness of FLULAVAL in children younger than 6 months have not been established.

8.5 Geriatric Use

In clinical trials, there were 330 subjects aged 65 years and older who received FLULAVAL; 142 of these subjects were aged 75 years and older. Hemagglutination inhibition antibody responses were lower in geriatric subjects than younger subjects after administration of FLULAVAL. [See Clinical Studies (14.2).] Solicited adverse events were similar in frequency to those reported in younger subjects [see Adverse Reactions (6.1)].

11 DESCRIPTION

FLULAVAL, Influenza Vaccine, for intramuscular use, is a trivalent, split-virion, inactivated influenza virus vaccine prepared from virus propagated in the allantoic cavity of embryonated hens’ eggs. Each of the influenza viruses is produced and purified separately. The virus is inactivated with ultraviolet light treatment followed by formaldehyde treatment, purified by centrifugation, and disrupted with sodium deoxycholate.

FLULAVAL is a sterile, opalescent, translucent to off-white injectable suspension in a phosphate-buffered saline solution that may sediment slightly. The sediment resuspends upon shaking to form a homogeneous suspension.

FLULAVAL has been standardized according to U.S. Public Health Service (USPHS) requirements for the 2025‑2026 influenza season and is formulated to contain 45 micrograms (mcg) hemagglutinin (HA) per 0.5-mL dose in the recommended ratio of 15 mcg HA of each of the following 3 strains: A/Victoria/4897/2022 (H1N1) IVR‑238, A/Croatia/10136RV/2023 (H3N2) X‑425A, and B/Austria/1359417/2021 BVR‑26 (B‑Victoria lineage).

FLULAVAL is formulated without preservatives and does not contain thimerosal.

Each 0.5-mL dose may also contain residual amounts of ovalbumin (≤0.3 mcg), formaldehyde (≤25 mcg), sodium deoxycholate (≤50 mcg), α-tocopheryl hydrogen succinate (≤240 mcg), and polysorbate 80 (≤665 mcg) from the manufacturing process. Antibiotics are not used in the manufacture of this vaccine.

The tip caps and plungers of the prefilled syringes are not made with natural rubber latex.

12 CLINICAL PHARMACOLOGY

12.1 Mechanism of Action

Specific levels of hemagglutination inhibition (HI) antibody titer post-vaccination with inactivated influenza virus vaccines have not been correlated with protection from influenza illness but the antibody titers have been used as a measure of vaccine activity. In some human challenge studies, antibody titers of ≥1:40 have been associated with protection from influenza illness in up to 50% of subjects.^1,2 Antibody against one influenza virus type or subtype confers little or no protection against another virus. Furthermore, antibody to one antigenic variant of influenza virus might not protect against a new antigenic variant of the same type or subtype. Frequent development of antigenic variants through antigenic drift is the virological basis for seasonal epidemics and the reason for the usual change of one or more new strains in each year’s influenza vaccine.

13 NONCLINICAL TOXICOLOGY

13.1 Carcinogenesis, Mutagenesis, Impairment of Fertility

FLULAVAL has not been evaluated for carcinogenic, mutagenic potential, or impairment of fertility in males.

14 CLINICAL STUDIES

The effectiveness of FLULAVAL was demonstrated based on clinical endpoint efficacy data for FLULAVAL QUADRIVALENT (Influenza Vaccine), clinical endpoint efficacy data for FLULAVAL, and on an evaluation of serum HI antibody responses to FLULAVAL and FLULAVAL QUADRIVALENT.

14.1 Efficacy against Influenza

Efficacy Trial in Children

The efficacy of FLULAVAL QUADRIVALENT was evaluated in Trial 6, a randomized, observer-blind, non-influenza vaccine-controlled trial conducted in 3 countries in Asia, 3 in Latin America, and 2 in the Middle East/Europe during the 2010-2011 influenza season. Healthy subjects aged 3 through 8 years were randomized (1:1) to receive FLULAVAL QUADRIVALENT (n = 2,584), containing A/California/7/2009 (H1N1), A/Victoria/210/2009 (H3N2), B/Brisbane/60/2008 (Victoria lineage), and B/Florida/4/2006 (Yamagata lineage) influenza strains, or HAVRIX (Hepatitis A Vaccine) (n = 2,584), as a control vaccine. Children with no history of influenza vaccination received 2 doses of FLULAVAL QUADRIVALENT or HAVRIX approximately 28 days apart. Children with a history of influenza vaccination received one dose of FLULAVAL QUADRIVALENT or HAVRIX. In the overall population, 52% were male; 60% were Asian, 5% were white, and 35% were of other racial/ethnic groups. The mean age of subjects was 5 years. Data for FLULAVAL QUADRIVALENT are relevant to FLULAVAL because both vaccines are manufactured using the same process and have overlapping compositions.

Efficacy of FLULAVAL QUADRIVALENT was assessed for the prevention of reverse transcriptase polymerase chain reaction (RT-PCR)-positive influenza A and/or B disease presenting as influenza-like illness (ILI). ILI was defined as a temperature ≥100°F in the presence of at least one of the following symptoms on the same day: cough, sore throat, runny nose, or nasal congestion. Subjects with ILI (monitored by passive and active surveillance for approximately 6 months) had nasal and throat swabs collected and tested for influenza A and/or B by RT-PCR. All RT-PCR-positive specimens were further tested in cell culture. Vaccine efficacy was calculated based on the ATP cohort for efficacy (Table 5).

Table 5. FLULAVAL QUADRIVALENT: Influenza Attack Rates and Vaccine Efficacy against Influenza A and/or B in Children Aged 3 through 8 Yearsa (According-to-Protocol Cohort for Efficacy)
 | Nb | nc | Influenza Attack Rate % (n/N) | Vaccine Efficacy; % (CI)
All RT-PCR-Positive Influenza
FLULAVAL QUADRIVALENT | 2,379 | 58 | 2.4 | 55.4d; (95% CI: 39.1, 67.3)
HAVRIXe | 2,398 | 128 | 5.3 | –
All Culture-Confirmed Influenzaf
FLULAVAL QUADRIVALENT | 2,379 | 50 | 2.1 | 55.9; (97.5% CI: 35.4, 69.9)
HAVRIXe | 2,398 | 112 | 4.7 | –
Antigenically Matched Culture-Confirmed Influenza
FLULAVAL QUADRIVALENT | 2,379 | 31 | 1.3 | 45.1g; (97.5% CI: 9.3, 66.8)
HAVRIXe | 2,398 | 56 | 2.3 | –

CI = Confidence Interval; RT-PCR = Reverse transcriptase polymerase chain reaction.
a Trial 6: NCT01218308.
b According‑to‑protocol cohort for efficacy included subjects who met all eligibility criteria, were successfully contacted at least once post‑vaccination, and complied with the protocol‑specified efficacy criteria.
c Number of influenza cases.
d Vaccine efficacy for FLULAVAL QUADRIVALENT met the pre‑defined criterion of >30% for the lower limit of the 2‑sided 95% CI.
e Hepatitis A Vaccine used as a control vaccine.
f Of 162 culture‑confirmed influenza cases, 108 (67%) were antigenically typed (87 matched; 21 unmatched); 54 (33%) could not be antigenically typed [but were typed by RT‑PCR and nucleic acid sequence analysis: 5 cases A (H1N1) (5 with HAVRIX), 47 cases A (H3N2) (10 with FLULAVAL QUADRIVALENT; 37 with HAVRIX), and 2 cases B Victoria (2 with HAVRIX)].
g Since only 67% of cases could be typed, the clinical significance of this result is unknown.

In an exploratory analysis by age, vaccine efficacy against RT-PCR-positive influenza A and/or B disease presenting as ILI was evaluated in subjects aged 3 through 4 years and 5 through 8 years; vaccine efficacy was 35.3% (95% CI: ‑1.3, 58.6) and 67.7% (95% CI: 49.7, 79.2), respectively. As the trial lacked statistical power to evaluate efficacy within age subgroups, the clinical significance of these results is unknown.

As a secondary objective in the trial, subjects with RT-PCR-positive influenza A and/or B were prospectively classified based on the presence of adverse outcomes that have been associated with influenza infection (defined as fever >102.2°F/39.0°C, physician-verified shortness of breath, pneumonia, wheezing, bronchitis, bronchiolitis, pulmonary congestion, croup and/or acute otitis media, and/or physician-diagnosed serious extra-pulmonary complications, including myositis, encephalitis, seizure and/or myocarditis).

The risk reduction of fever >102.2°F/39.0°C associated with RT-PCR-positive influenza was 71.0% (95% CI: 44.8, 84.8) based on the ATP cohort for efficacy [FLULAVAL QUADRIVALENT (n = 12/2,379); HAVRIX (n = 41/2,398)]. The other pre-specified adverse outcomes had too few cases to calculate a risk reduction. The incidence of these adverse outcomes is presented in Table 6.

Table 6. FLULAVAL QUADRIVALENT: Incidence of Adverse Outcomes Associated with RT-PCR-Positive Influenza in Children Aged 3 through 8 Yearsa (Total Vaccinated Cohort)b
 | FLULAVAL; QUADRIVALENT; n = 2,584 |  |  | HAVRIXc; n = 2,584
Adverse Outcomed | Number of Events | Number of Subjectse | % | Number of Events | Number of Subjectse | %
Fever >102.2°F/39.0°C | 16f | 15 | 0.6 | 51f | 50 | 1.9
Shortness of breath | 0 | 0 | 0 | 5 | 5 | 0.2
Pneumonia | 0 | 0 | 0 | 3 | 3 | 0.1
Wheezing | 1 | 1 | 0 | 1 | 1 | 0
Bronchitis | 1 | 1 | 0 | 1 | 1 | 0
Pulmonary congestion | 0 | 0 | 0 | 1 | 1 | 0
Acute otitis media | 0 | 0 | 0 | 1 | 1 | 0
Bronchiolitis | 0 | 0 | 0 | 0 | 0 | 0
Croup | 0 | 0 | 0 | 0 | 0 | 0
Encephalitis | 0 | 0 | 0 | 0 | 0 | 0
Myocarditis | 0 | 0 | 0 | 0 | 0 | 0
Myositis | 0 | 0 | 0 | 0 | 0 | 0
Seizure | 0 | 0 | 0 | 0 | 0 | 0
a Trial 6: NCT01218308.
b Total vaccinated cohort included all vaccinated subjects for whom data were available.
c Hepatitis A Vaccine used as a control vaccine.
d In subjects who presented with more than one adverse outcome, each outcome was counted in the respective category.
e Number of subjects presenting with at least one event in each group.
f One subject in each group had sequential influenza due to influenza type A and type B viruses.

Efficacy Trial in Adults

The efficacy of FLULAVAL was evaluated in a randomized, double-blind, placebo-controlled trial conducted in the United States during the 2005-2006 and 2006-2007 influenza seasons (Trial 3). Efficacy of FLULAVAL was defined as the prevention of culture-confirmed influenza A and/or B cases, for vaccine antigenically matched strains, compared with placebo. Healthy subjects aged 18 through 49 years were randomized (1:1); a total of 3,783 subjects received FLULAVAL and 3,828 subjects received placebo [see Adverse Reactions (6.1)]. Subjects were monitored for influenza-like illnesses (ILI) starting 2 weeks post-vaccination and for duration of approximately 7 months thereafter. Culture-confirmed influenza was assessed by active and passive surveillance of ILI. Influenza-like illness was defined as illness sufficiently severe to limit daily activity and including cough, and at least one of the following: Fever >99.9°F, nasal congestion or runny nose, sore throat, muscle aches or arthralgia, headache, feverishness or chills. After an episode of ILI, nose and throat swab samples were collected for analysis; attack rates and vaccine efficacy were calculated using the per protocol cohort (Table 7). Of note, the 1.2% attack rate in the placebo group for culture-confirmed, antigenically matched strains was lower than expected, contributing to a wide confidence interval for the estimate of vaccine efficacy.

Table 7. FLULAVAL: Influenza Attack Rates and Vaccine Efficacy against Culture-Confirmed Influenza in Adults Aged 18 through 49 Yearsa (Per Protocol Cohort)
 |  |  | Influenza Attack Rates | Vaccine Efficacy
 | Nb | nc | % (n/N) | % | 97.5% CI; Lower Limit
Antigenically Matched Strains
FLULAVAL | 3,714 | 23 | 0.6 | 46.3 | 9.8d
Placebo | 3,768 | 45 | 1.2 | – | –
All Culture-Confirmed Influenza (Matched, Unmatched, and Untyped)
FLULAVAL | 3,714 | 30 | 0.8 | 49.3 | 20.3
Placebo | 3,768 | 60 | 1.6 | – | –

CI = Confidence Interval.
a Trial 3: NCT00216242.
b Per Protocol Cohort for efficacy included subjects with no protocol deviations considered to compromise efficacy data.
c Number of influenza cases.
d Lower limit of the one‑sided 97.5% CI for vaccine efficacy against influenza due to antigenically matched strains was less than the pre‑defined success criterion of ≥35%.

14.2 Immunological Evaluation

Adults

Trial 1 was a randomized, blinded, active-controlled U.S. trial performed in healthy adults aged 18 through 64 years (N = 1,000). A total of 721 subjects received FLULAVAL, and 279 received a U.S.‑licensed trivalent, inactivated influenza vaccine, FLUZONE (manufactured by Sanofi Pasteur Inc.), intramuscularly; 959 subjects had complete serological data and no major protocol deviations [see Adverse Reactions (6.1)].

Analyses of immunogenicity (Table 8) were performed for each hemagglutinin (HA) antigen contained in the vaccine: 1) assessment of the lower bounds of 2‑sided 95% confidence intervals for the proportion of subjects with HI antibody titers of ≥1:40 after vaccination, and 2) assessment of the lower bounds of 2-sided 95% confidence intervals for rates of seroconversion (defined as a 4‑fold increase in post-vaccination HI antibody titer from pre-vaccination titer ≥1:10, or an increase in titer from <1:10 to ≥1:40). The pre-specified success criteria for HI titer ≥1:40 was 70% and for seroconversion rate was 40%. The lower limit of the 2-sided 95% CI for the percentage of subjects who achieved an HI titer of ≥1:40 exceeded the pre-defined criteria for the A strains. The lower limit of the 2-sided 95% CI for the percentage of subjects who achieved seroconversion exceeded the pre-defined criteria for all 3 strains.

Table 8. Immune Responses to Each Antigen 21 Days after Vaccination with FLULAVALa in Adults Aged 18 through 64 Years (Per Protocol Cohort)b
 | FLULAVAL; N = 692; % of Subjects (95% CI)
HI titers ≥1:40c | Pre-Vaccination | Post-Vaccination
A/New Caledonia/20/99 (H1N1) | 24.6 | 96.5 (94.9, 97.8)
A/Wyoming/03/03 (H3N2) | 58.7 | 98.7 (97.6, 99.4)
B/Jiangsu/10/03 | 5.4 | 62.9 (59.1, 66.5)
Seroconversiond,e to:
A/New Caledonia/20/99 (H1N1) | 85.6 (82.7, 88.1)
A/Wyoming/03/03 (H3N2) | 79.3 (76.1, 82.3)
B/Jiangsu/10/03 | 58.4 (54.6, 62.1)

HI = hemagglutination inhibition; CI = Confidence Interval.
a Results obtained following vaccination with FLULAVAL manufactured for the 2004–2005 season.
b Per Protocol Cohort for immunogenicity included subjects with complete pre- and post‑dose HI titer data and no major protocol deviations.
c The pre‑specified success criteria for HI titer ≥1:40 was 70%.
d Seroconversion defined as a 4‑fold increase in post‑vaccination HI antibody titers from pre‑vaccination titer ≥1:10, or an increase in titer from <1:10 to ≥1:40.
e The pre‑specified success criteria for seroconversion rate was 40%.

Trial 2 (Immunogenicity Non-Inferiority): In a randomized, double-blind, active-controlled U.S. trial, immunological non-inferiority of FLULAVAL was compared with a U.S.‑licensed trivalent, inactivated influenza vaccine, FLUZONE, manufactured by Sanofi Pasteur Inc. A total of 1,225 adults aged 50 years and older in stable health were randomized to receive FLULAVAL or the comparator vaccine intramuscularly [see Adverse Reactions (6.1)].

Analyses of immunogenicity were performed for each HA antigen contained in the vaccines: 1) assessment of the lower bounds of 2‑sided 95% confidence intervals for the geometric mean antibody titer (GMT) ratio (FLULAVAL/comparator), and 2) assessment of the lower bounds of 2‑sided 95% confidence intervals for seroconversion rates (defined as a 4‑fold increase in post‑vaccination HI antibody titer from pre-vaccination titer ≥1:10, or an increase in titer from <1:10 to ≥1:40). Non-inferiority of FLULAVAL to the comparator vaccine was established for all 6 co–primary endpoints (Table 9). Within each age stratum, immunogenicity results were similar between the groups.

Table 9. Immune Responses to Each Antigen 21 Days after Vaccination with FLULAVAL Versus Comparator Influenza Vaccine in Adults Aged 50 Years and Oldera (Per Protocol Cohort)b
 | FLULAVAL; n = 592 | Active Comparatorc; n = 595
GMTs Against | GMT; (95% CI) | GMT; (95% CI) | GMT Ratiod; (95% CI)
A/New Caledonia/20/99 (H1N1) | 113.4; (104.7, 122.8) | 110.2; (101.8, 119.3) | 1.03; (0.92, 1.15)
A/New York/55/04 (H3N2) | 223.9; (199.5, 251.3) | 214.6; (191.3, 240.7) | 1.04; (0.89, 1.23)
B/Jiangsu/10/03 | 82.3; (74.7, 90.6) | 97.1; (88.2, 106.8) | 0.85; (0.74, 0.97)
Seroconversione to: | % of Subjects; (95% CI) | % of Subjects; (95% CI) | Difference in Seroconversion Ratesf; (95% CI)
A/New Caledonia/20/99 (H1N1) | 34; (30.0, 37.6) | 32; (28.3, 35.9) | 2; (-3.7, 7.0)
A/New York/55/04 (H3N2) | 83; (80.3, 86.3) | 82; (78.4, 84.6) | 1; (-2.6, 6.1)
B/Jiangsu/10/03 | 53; (49.0, 57.1) | 56; (51.6, 59.6) | -3; (-8.3, 3.1)

GMT = Geometric mean antibody titer; CI = Confidence Interval.
a Results obtained following vaccination with influenza vaccines manufactured for the 2005‑2006 season.
b Per Protocol Cohort for immunogenicity included subjects with complete pre- and post‑dose HI titer data and no major protocol deviations.
c U.S.‑licensed trivalent, inactivated influenza vaccine (manufactured by Sanofi Pasteur Inc.).
d FLULAVAL met non‑inferiority criteria based on GMTs (lower limit of 2‑sided 95% CI for GMT ratio [FLULAVAL/comparator vaccine] ≥0.67).
e Seroconversion defined as a 4‑fold increase in post‑vaccination HI antibody titer from pre‑vaccination titer ≥1:10, or an increase in titer from <1:10 to ≥1:40.
f FLULAVAL met non‑inferiority criteria based on seroconversion rates (lower limit of 2‑sided 95% CI for difference of FLULAVAL minus the comparator vaccine ≥‑10%).

Children

In Trial 4, the immune response of FLULAVAL (n = 987) was compared to FLUZONE, a U.S.‑licensed trivalent, inactivated influenza vaccine (n = 979), manufactured by Sanofi Pasteur Inc., in an observer-blind, randomized trial in children aged 3 through 17 years. The immune responses to each of the antigens contained in FLULAVAL formulated for the 2009-2010 season were evaluated in sera obtained after one or 2 doses of FLULAVAL and were compared with those following the comparator influenza vaccine [see Adverse Reactions (6.1)].

The non‑inferiority endpoints were GMTs adjusted for baseline, and the percentage of subjects who achieved seroconversion, defined as at least a 4‑fold increase in serum HI titer over baseline to ≥1:40, following vaccination, performed on the According‑to‑Protocol (ATP) cohort. FLULAVAL was non-inferior to the comparator influenza for all strains based on adjusted GMTs and seroconversion rates (Table 10).

Table 10. Immune Responses to Each Antigen 28 Days after Last Vaccination with FLULAVAL Versus Comparator Influenza Vaccine in Children Aged 3 through 17 Yearsa (According-to-Protocol Cohort for Immunogenicity)b
 | FLULAVAL | Active Comparatorc
GMTs Against | n = 987; (95% CI) | n = 979; (95% CI) | GMT Ratiod; (95% CI)
A/Brisbane (H1N1) | 320.9; (298.3, 345.2) | 329.4; (306.8, 353.7) | 1.03; (0.94, 1.13)
A/Uruguay (H3N2) | 414.7; (386.5, 444.9) | 451.9; (423.8, 481.8) | 1.05; (0.96, 1.13)
B/Brisbane | 213.7; (198.5, 230.1) | 200.2; (186.1, 215.3) | 0.93; (0.85, 1.02)
Seroconversione to: | n = 987; %; (95% CI) | n = 978; %; (95% CI) | Difference in Seroconversion Ratef; (95% CI)
A/Brisbane (H1N1) | 59.8; (56.6, 62.9) | 58.2; (55.0, 61.3) | -1.6; (-5.9, 2.8)
A/Uruguay (H3N2) | 68.2; (65.2, 71.1) | 66.2; (63.1, 69.1) | -2.0; (-6.1, 2.1)
B/Brisbane | 81.1; (78.5, 83.5) | 78.6; (75.9, 81.2) | -2.4; (-6.0, 1.1)

GMT = Geometric mean antibody titer; CI = Confidence Interval.
a Results obtained following vaccination with influenza vaccines formulated for the 2009-2010 season.
b According‑to‑protocol cohort for immunogenicity included all evaluable subjects for whom assay results were available after vaccination for at least one trial vaccine antigen.
c U.S.‑licensed trivalent, inactivated influenza vaccine (Sanofi Pasteur Inc.).
d FLULAVAL met non‑inferiority criteria based on GMTs (upper limit of 2‑sided 95% CI for GMT ratio [comparator vaccine/FLULAVAL] ≤1.5).
e Seroconversion defined as a 4‑fold increase in post‑vaccination HI antibody titer from pre‑vaccination titer ≥1:10, or an increase in titer from <1:10 to ≥1:40.
f FLULAVAL met non‑inferiority criteria based on seroconversion rates (upper limit of 2‑sided 95% CI for difference of the comparator vaccine minus FLULAVAL ≤10%).

Trial 5 was a randomized, observer-blind, active-controlled trial in children aged 6 through 35 months which was conducted in the United States and Mexico. In this trial, subjects received 0.5 mL of FLULAVAL QUADRIVALENT containing 15 mcg HA of each of the four influenza strains included in the vaccine (n = 1,207); or 0.25 mL of control vaccine FLUZONE QUADRIVALENT (Influenza Vaccine) containing 7.5 mcg HA of each of the four influenza strains included in the vaccine (n = 1,217) [see Adverse Reactions (6.1)].

Immune responses, specifically HI antibody titers to each virus strain in the vaccine, were evaluated in sera obtained 28 days following completion of vaccination regimen. Previously vaccinated children received one dose and previously unvaccinated children (i.e., unprimed individuals) received 2 doses 4 weeks apart of FLULAVAL QUADRIVALENT or the comparator. The immunogenicity endpoints were GMTs adjusted for baseline, and the percentage of subjects who achieved seroconversion, defined as a pre-vaccination HI titer of <1:10 with a post-vaccination titer ≥1:40 or at least a 4‑fold increase in serum HI titer over baseline to ≥1:40, following vaccination, performed on the ATP cohort. FLULAVAL QUADRIVALENT was non-inferior to the comparator for all 4 vaccine strains based on adjusted GMTs and seroconversion rates (Table 11).

Table 11. Non-inferiority of FLULAVAL QUADRIVALENT Relative to Comparator Quadrivalent Influenza Vaccine at 28 Days Post-Vaccination in Children Aged 6 through 35 Monthsa (According-to-Protocol Cohort for Immunogenicity)b
 | FLULAVAL QUADRIVALENTc | Active Comparatord
Adjusted Geometric Mean Titers Against | n = 972-974 | n = 980
A/California/07/2009 (H1N1) | 99.6e | 85.1
A/Texas/50/2012; (H3N2) | 99.8e | 84.6
B/Massachusetts/02/2012 (Yamagata lineage) | 258.1e | 167.3
B/Brisbane/60/2008; (Victoria lineage) | 54.5e | 33.7
Seroconversionf to: | n = 972-974; %; (95% CI) | n = 980; %; (95% CI)
A/California/07/2009 (H1N1) | 73.7e; (70.8, 76.4) | 67.3; (64.3, 70.3)
A/Texas/50/2012; (H3N2) | 76.1e; (73.3, 78.8) | 69.4; (66.4, 72.3)
B/Massachusetts/02/2012 (Yamagata lineage) | 85.5e; (83.2, 87.7) | 73.8; (70.9, 76.5)
B/Brisbane/60/2008; (Victoria lineage) | 64.9e; (61.8, 67.9) | 48.5; (45.3, 51.6)

CI = Confidence Interval.
a Trial 5: NCT02242643.
b According‑to‑protocol cohort for immunogenicity included all evaluable subjects for whom assay results were available after vaccination for at least one trial vaccine antigen.
c A 0.5‑mL dose containing 15 mcg each of A/California/07/2009 (H1N1), A/Texas/50/2012 (H3N2), B/Massachusetts/02/2012 (Yamagata lineage), and B/Brisbane/60/2008 (Victoria lineage).
d A 0.25‑mL dose of U.S.‑licensed quadrivalent, inactivated influenza vaccine (manufactured by Sanofi Pasteur Inc.) containing 7.5 mcg each of A/California/07/2009 (H1N1), A/Texas/50/2012 (H3N2), B/Massachusetts/02/2012 (Yamagata lineage), and B/Brisbane/60/2008 (Victoria lineage).
e Non‑inferior to the comparator vaccine based on adjusted GMTs [upper limit of the 2‑sided 95% CI for the GMT ratio (comparator/FLULAVAL QUADRIVALENT) ≤1.5] and seroconversion rates (upper limit of the 2‑sided 95% CI on difference of comparator vaccine minus FLULAVAL QUADRIVALENT ≤10%).
f Seroconversion defined as a 4‑fold increase in post‑vaccination antibody titer from pre‑vaccination titer ≥1:10, or an increase in titer from <1:10 to ≥1:40.

15 REFERENCES

1. Hannoun C, Megas F, Piercy J. Immunogenicity and protective efficacy of influenza vaccination. Virus Res 2004;103:133-138.
2. Hobson D, Curry RL, Beare AS, et al. The role of serum haemagglutination-inhibiting antibody in protection against challenge infection with influenza A2 and B viruses. J Hyg Camb 1972;70:767-777.

16 HOW SUPPLIED/STORAGE AND HANDLING

FLULAVAL is available in 0.5-mL single-dose, disposable, prefilled TIP-LOK syringes (Luer Lock syringes) packaged without needles. TIP-LOK syringes are to be used with Luer Lock compatible needles. The tip cap and rubber plunger stopper of the prefilled syringe are not made with natural rubber latex.

NDC 19515-904-41 Syringe in Package of 10: NDC 19515-904-52

Store refrigerated between 2º and 8ºC (36º and 46ºF). Do not freeze. Discard if the vaccine has been frozen. Store in the original package to protect from light.

17 PATIENT COUNSELING INFORMATION

Provide the following information to the vaccine recipient or guardian:

- Inform of the potential benefits and risks of immunization with FLULAVAL.
- Educate regarding potential side effects, emphasizing that: (1) FLULAVAL contains non-infectious killed viruses and cannot cause influenza, and (2) FLULAVAL is intended to provide protection against illness due to influenza viruses only, and cannot provide protection against all respiratory illness.
- Give the Vaccine Information Statements, which are required by the National Childhood Vaccine Injury Act of 1986 prior to each immunization. These materials are available free of charge at the Centers for Disease Control and Prevention (CDC) website (www.cdc.gov/vaccines).
- Instruct that annual revaccination is recommended.

FLULAVAL, TIP-LOK, and HAVRIX are trademarks owned by or licensed to the GSK group of companies. The other brands listed are trademarks owned by or licensed to their respective owners and are not owned by or licensed to the GSK group of companies. The makers of these brands are not affiliated with and do not endorse the GSK group of companies or its products.

Manufactured by ID Biomedical Corporation of Quebec

Quebec City, QC, Canada, U.S. License 1739

Distributed by GlaxoSmithKline

Durham, NC 27701

©2025 the GSK group of companies or its licensor.

FLV:18PI

PACKAGE LABEL

Principal Display Panel

NDC 19515-904-52

FLULAVAL

Influenza Vaccine

2025/2026 Formula

Rx only

GSK

For 6 Months of Age and Older

10 Disposable Single-Dose Prefilled TIP-LOK Syringes each containing one 0.5-mL dose

TIP-LOK syringes to be used with Luer Lock compatible needles

NEEDLES NOT INCLUDED

Flulaval

Made in Canada

©2025 GSK group of companies or its licensor.

Rev. 3/25

523685